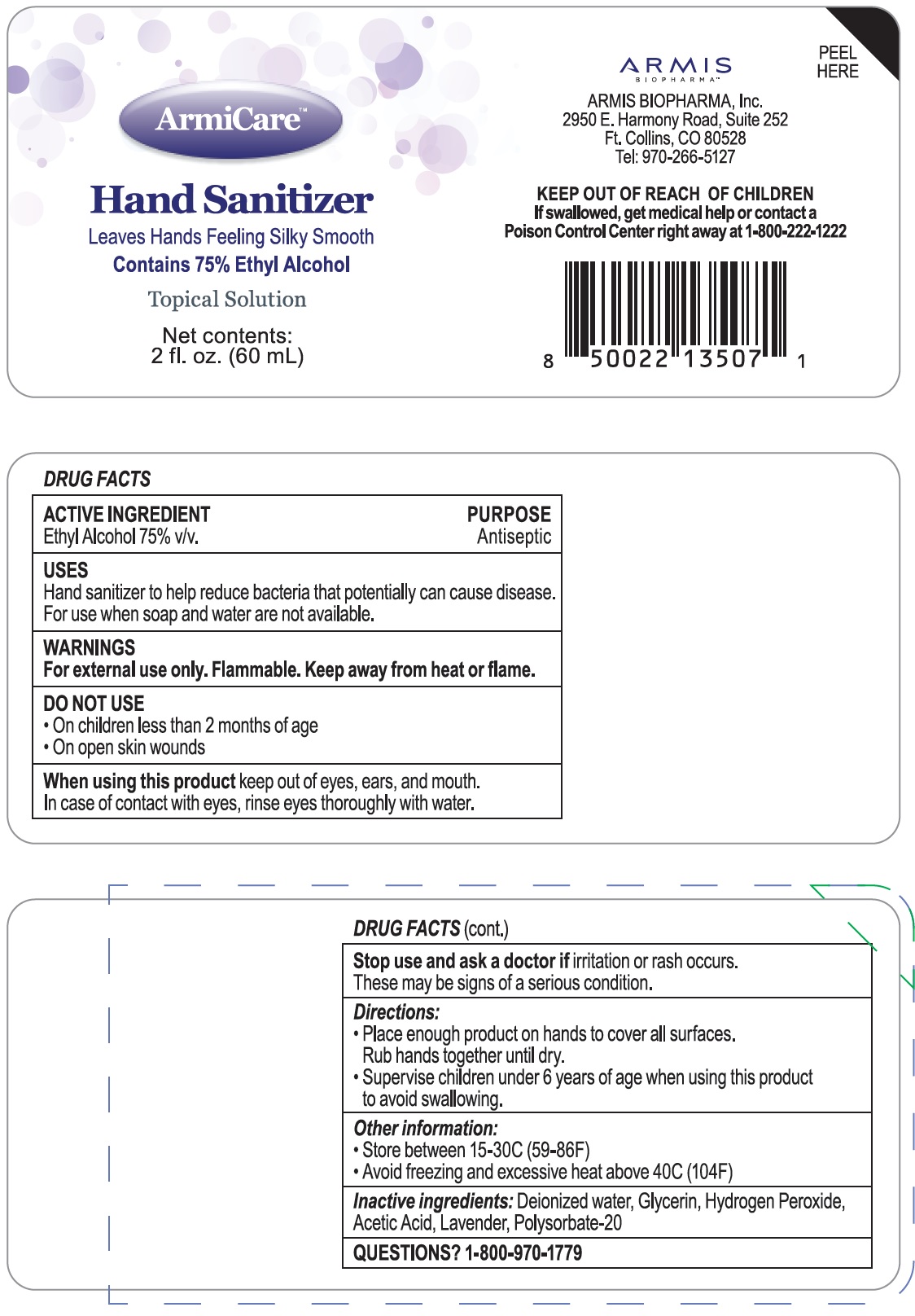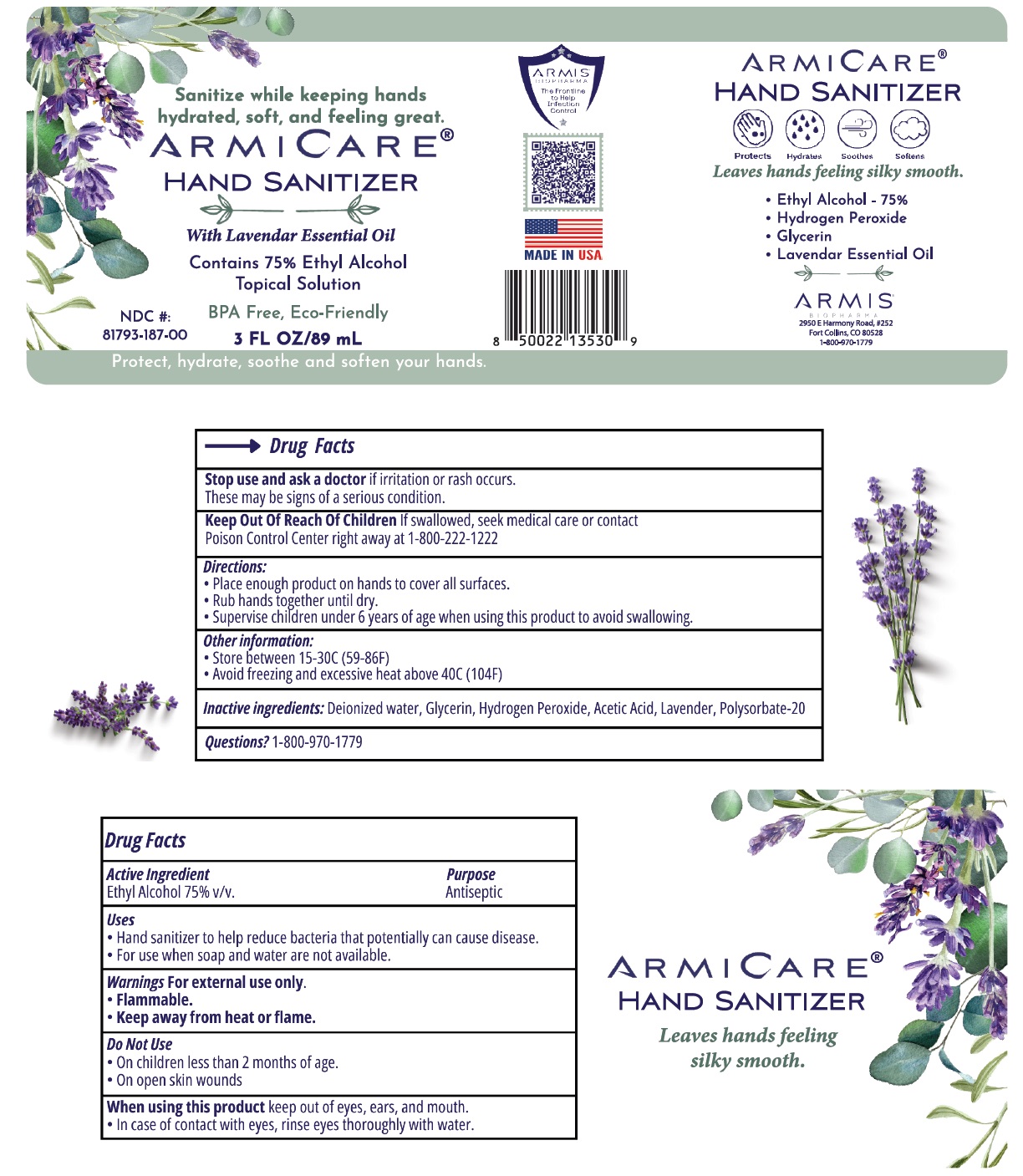 DRUG LABEL: ArmiCare Hand Sanitizer
NDC: 81793-187 | Form: LIQUID
Manufacturer: Armis Biopharma, Inc
Category: otc | Type: HUMAN OTC DRUG LABEL
Date: 20240206

ACTIVE INGREDIENTS: ALCOHOL 75 mL/100 mL
INACTIVE INGREDIENTS: WATER; GLYCERIN; HYDROGEN PEROXIDE; ACETIC ACID; LAVANDULA ANGUSTIFOLIA SUBSP. ANGUSTIFOLIA FLOWER; POLYSORBATE 20

ArmiCare Hand Sanitizer

ACTIVE INGREDIENT

Ethyl Alcohol 75% v/v.

PURPOSE

Antiseptic

USES

Hand sanitizer to help reduce bacteria that potentially can cause disease. For use when soap and water are not available.

WARNINGS

For external use only. Flammable. Keep away from heat or flame.

DO NOT USE

- On children less than 2 months of age
- On open skin wounds

When using this product

keep out of eyes, ears, and mouth. In case of contact with eyes, rinse eyes thoroughly with water.

Stop use and ask a doctor if

irritation or rash occurs. These may be signs of a serious condition.

KEEP OUT OF REACH OF CHILDREN

If swallowed, get medical help or contact a Poison Control Center right away at 1-800-222-1222

Directions:

- Place enough product on hands to cover all surfaces. Rub hands together until dry.
- Supervise children under 6 years of age when using this product to avoid swallowing.

Other information:

- Store between 15-30C (59-86F)
- Avoid freezing and excessive heat above 40C (104F)

Inactive ingredients:

Deionized water, Glycerin, Hydrogen Peroxide, Acetic Acid, Lavender, Polysorbate-20

QUESTIONS?

1-800-970-1779